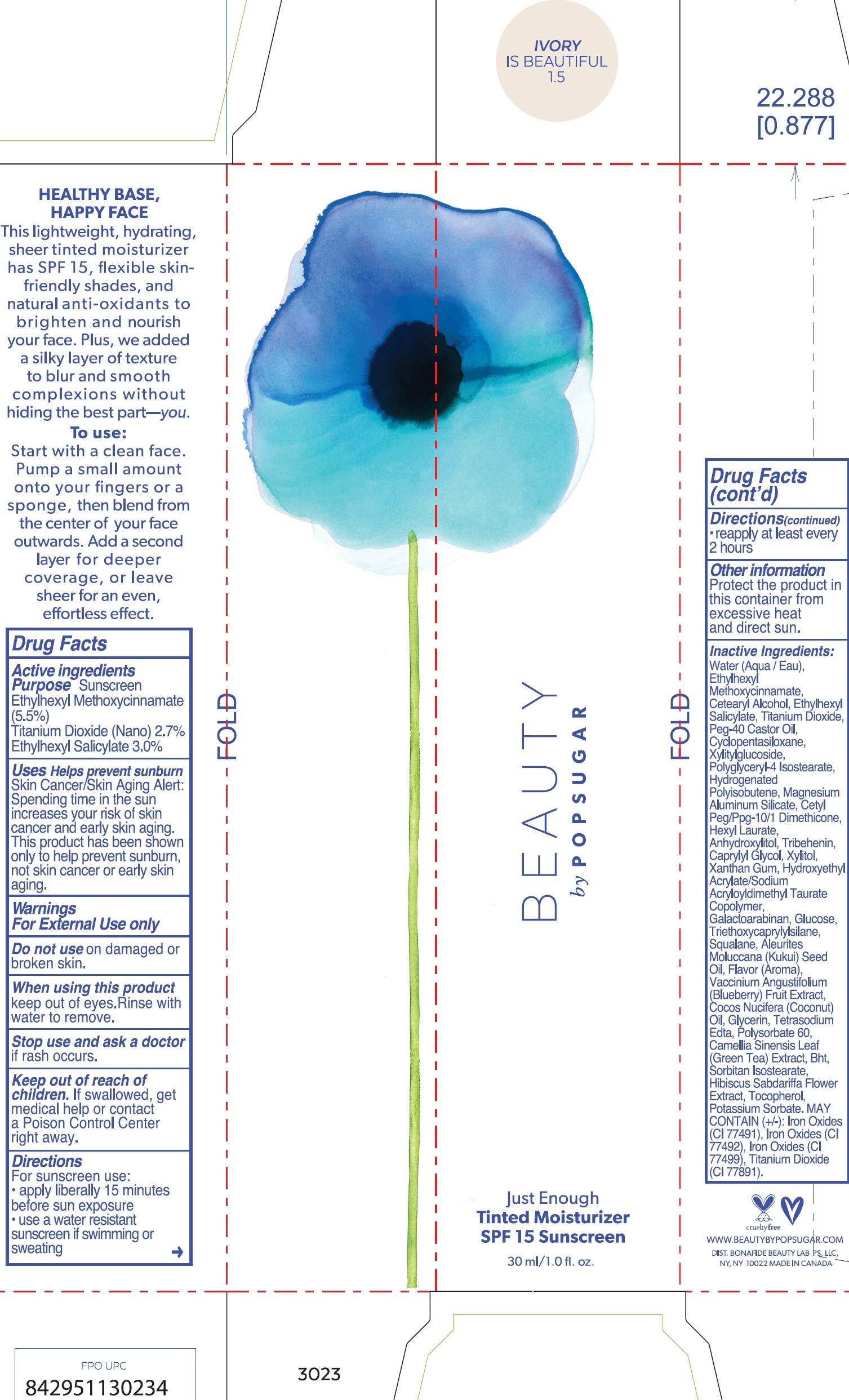 DRUG LABEL: Just Enough SPF 15 Tinted Moisturizer
NDC: 72112-017 | Form: CREAM
Manufacturer: Bona Fide Beauty Lab PS LLC
Category: otc | Type: HUMAN OTC DRUG LABEL
Date: 20180417

ACTIVE INGREDIENTS: OCTINOXATE 55 mg/1 mL; TITANIUM DIOXIDE 27 mg/1 mL; OCTISALATE 30 mg/1 mL
INACTIVE INGREDIENTS: WATER; CETOSTEARYL ALCOHOL; PEG-40 CASTOR OIL; CYCLOMETHICONE 5; XYLITYLGLUCOSIDE; POLYGLYCERYL-4 ISOSTEARATE; HYDROGENATED POLYBUTENE (1300 MW); MAGNESIUM ALUMINUM SILICATE; HEXYL LAURATE; ANHYDROXYLITOL; TRIBEHENIN; CAPRYLYL GLYCOL; XYLITOL; XANTHAN GUM; GALACTOARABINAN; DEXTROSE, UNSPECIFIED FORM; TRIETHOXYCAPRYLYLSILANE; SQUALANE; KUKUI NUT OIL; METHYL SALICYLATE; LOWBUSH BLUEBERRY; COCONUT OIL; GLYCERIN; EDETATE SODIUM; POLYSORBATE 60; GREEN TEA LEAF; BUTYLATED HYDROXYTOLUENE; SORBITAN ISOSTEARATE; HIBISCUS SABDARIFFA FLOWER; TOCOPHEROL; POTASSIUM SORBATE

Just Enough SPF 15 Tinted Moisturizer Ivory is Beautiful

Active ingredients

Ethylhexyl Methoxycinnamate (5.5%)

Titanium Dioxide (Nano) 2.7%

Ethylhexyl Salicylate 3.0%

Purpose

Sunscreen

Uses

Helps prevent sunburn Skin Cancer/Skin Aging Alert: Spending time in the sun increases your risk of skin cancer and early sking aging. This product has been shown only to help prevent sunburn, not skin cancer or early skin aging.

Warnings

For Exteranl Use only

Do not use

on damaged or broken skin.

When using this product

keep out of eyes. Rinse with water to remove.

Stop use and ask a doctor

if rash occur.

Keep out of reach of children.

If swallowed, get medical help or contact a Poison Control Center right away.

Directions

For sunscreen use:

- apply liberally 15 minutes before sun exposure
- use a water resistant sunscreen if swimming or sweating
- reapply at least every 2 hours

Other information

Protect the product in this container from excessive heat and direct sun.

Inacitive Ingredients:

Water (Aqua), Ethylhexyl Methoxycinnamate, Cetearyl Alcohol, Ethylhexyl Salicylate, Titanium Dioxide, Peg-40 Castor Oil, Cyclopentasiloxane, Xylitylglucoside, Polyglyceryl-4 Isostearate, Hydrogenated Polyisobutene, Magnesium Aluminum Silicate, Cetyl Peg/Ppg-10/1 Dimethicone, Hexyl Laurate, Anhydroxylitol, Tribehenin, Caprylyl Glycol, Xylitol, Xanthan Gum, Hydorxyethyl Acrylate/Sodium Acryloyldimethyl Taurate Copolymer, Galactoarabinan, GLucose, Triethoxycaprylylsilane, Squalane, Aleurites Moluccana (Kukui) Seed Oil, Flavor (Aroma), Vaccinium Angustifolium (Blueberry) Fruit Extract, Cocos Nucifera (Coconut) Oil, Glycerin, Tetrasodium Edta, Polysorbate 60, Camellia Sinensis Leaf (Green Tea) Extract, Bht, Sorbitan Isostearate, Hibiscus Sabdariffa Flower Extract, Tocopherol, Potassium Sorbate. MAY CONTAIN (+/-): Iron Oxides (CI 77491), Iran Oxides (CI 77492), Iron Oxides (CI 77499), Titanium Dioxide (CI 77891).